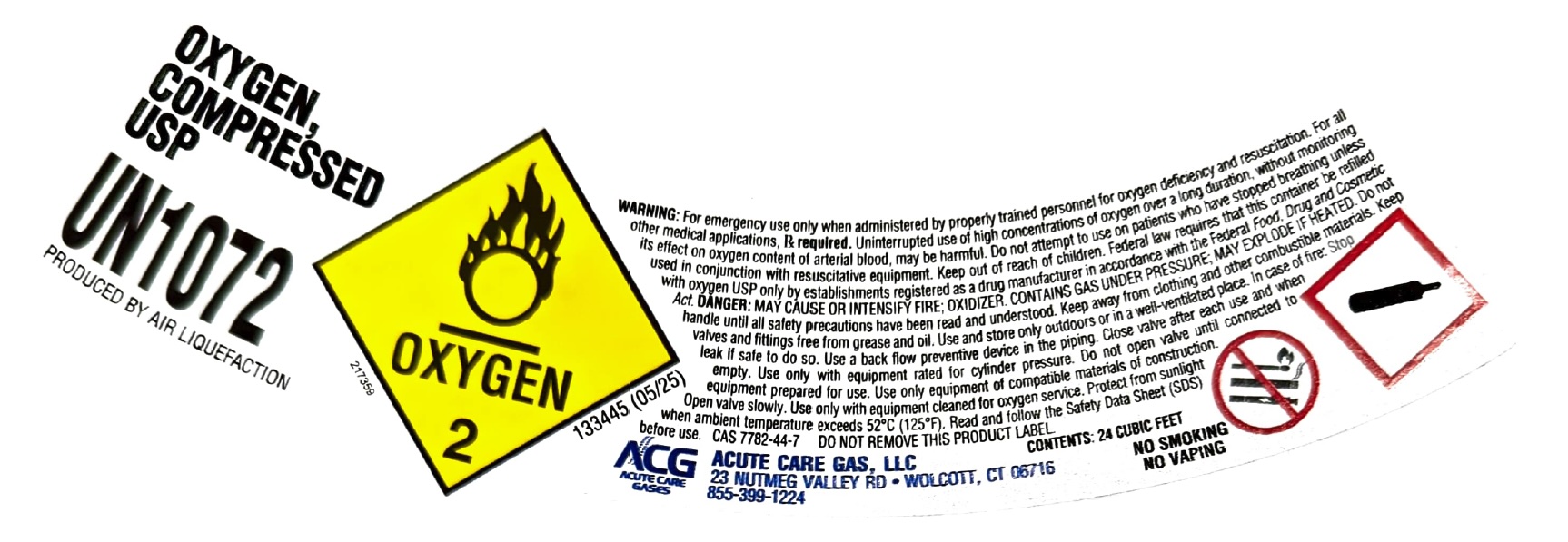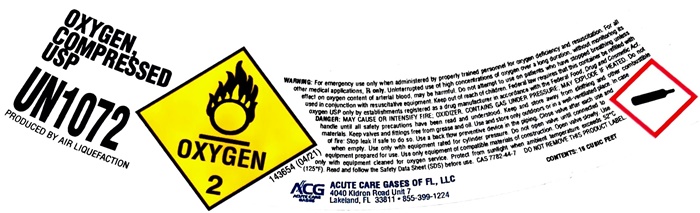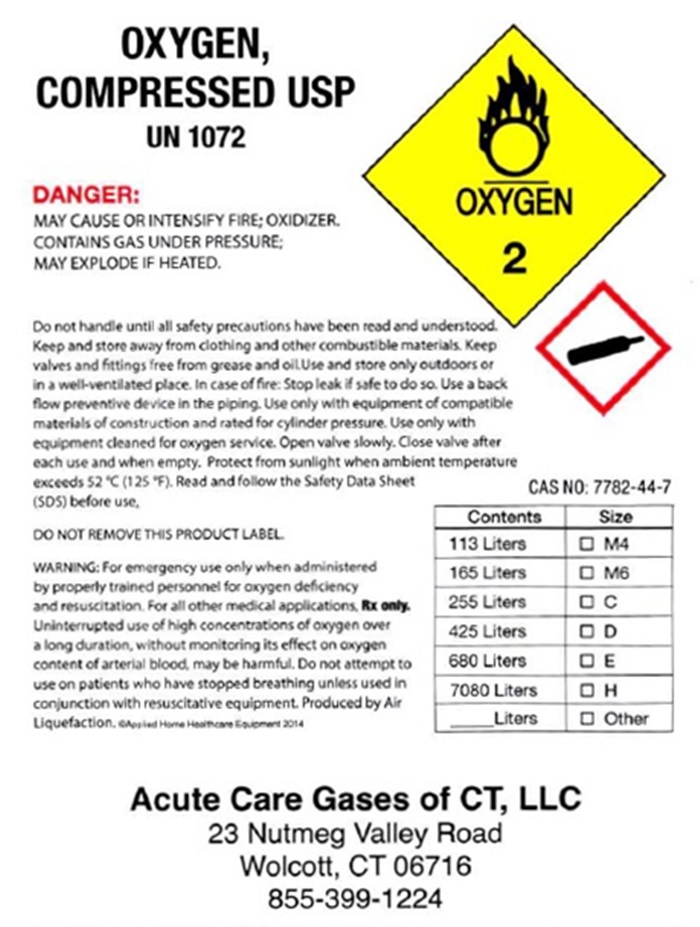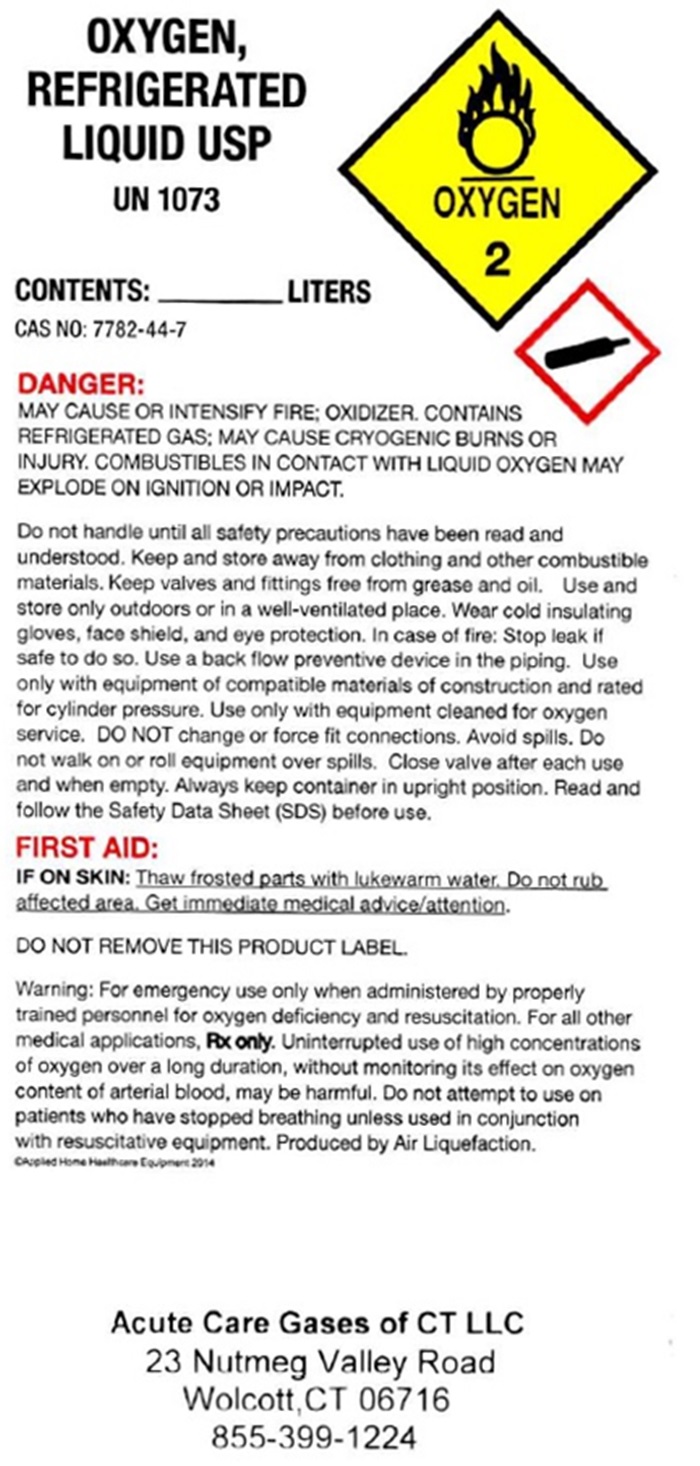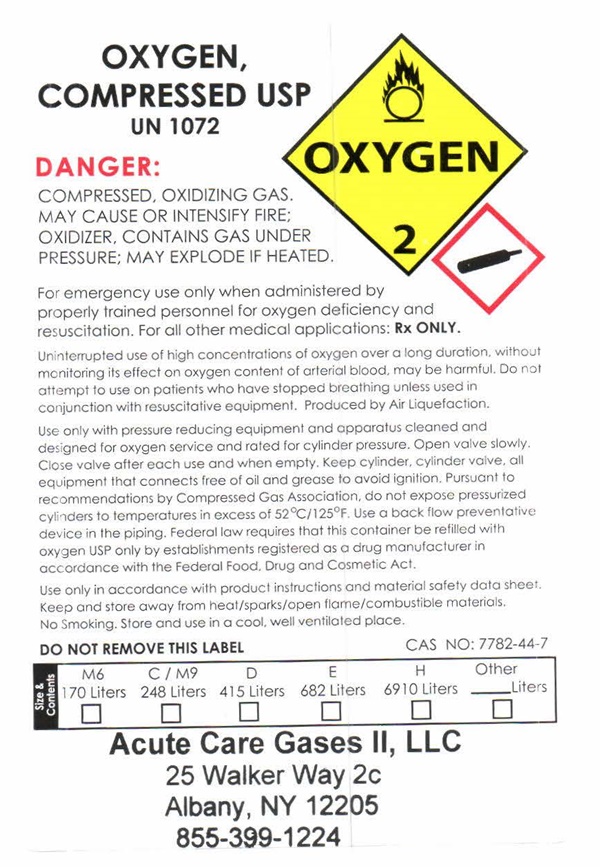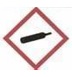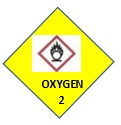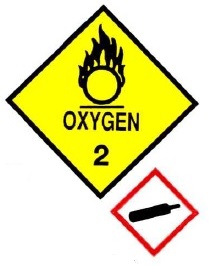 DRUG LABEL: Oxygen
NDC: 69240-001 | Form: GAS
Manufacturer: ACUTE CARE GAS LLC
Category: prescription | Type: HUMAN PRESCRIPTION DRUG LABEL
Date: 20250627

ACTIVE INGREDIENTS: OXYGEN 99 L/100 L

Oxygen

Oxygen

OXYGEN, COMPRESSED USP UN1072 OXYGEN 2

DANGER: COMPRESSED, OXIDING GAS. MAY CAUSE OR INTENSIFY FIRE; OXIDIZER, CONTAINS GAS UNDER PRESSURE; MAY EXPLODE IF HEATED.

For emergency use only when administered by properly trained personnel for oxygen deficiency and resuscitation. For all other medical applications. Rx only.

Uninterrupted use of high concentrations of oxygen over a long duration without monitoring its effect on oxygen content of arterial blood, may be harmful. Do not attempt to use on patients who have stopped breathing unless used in conjunction with resuscitative equipment. Produced by Air Liquefaction.

Use only with pressure reducing equipment and apparatus cleaned and designed for oxygen service and rated for cylinder pressure. Open valve slowly. Close valve after each use and when empty. Keep cylinder, cylinder valve, all equipment that connects free of oil and grease to avoid ignition Pursuant to recommendations by Compressed Gas Association, do not expose pressurized cylinders to temperatures in excess of 52OC/125OF. Use a back-flow preventative device in the piping. Federal law requires that the container be refilled with oxygen USP only by establishments registered as a drug manufacturer in accordance with the Federal Food, Drug and Cosmetic Act.

Use only in accordance with product instructions and material safety data sheet. Keep and store away from heat/sparks/open flame/combustible materials. No smoking. Store and use in a cool, well ventilated place.

DO NOT REMOVE THIS LABEL CAS 7782-44-7

Size & Contents

M6 C / M9 D E H Other

170 Liters 248 Liters 415 Liters 682 Liters 6910 Liters ____Liters

□ □ □ □ □ □

Acute Care Gases II, LLC

25 Walker Way 2c

Albany, NY 12205

855-399-1224

Oxygen Refridgerated

OXYGEN, REFRIGERATED LIQUID USP UN1073

OXYGEN, U.S.P.

OXYGEN 2

Contents __________________ Liters

CAS NO: 7782-44-7

DANGER: MAY CAUSE OR INTENSIFY FIRE; OXIDER, CONTAINS REFRIGERATED GAS; MAY CAUSE CRYOGENIC BURNS OR INJURY. COMBUSTIBELS IN CONTACT WITH LIQUID OXYGEN MAY EXPLODE ON IGNITION OR IMPACT.

Do not handle until all safety precautions have been read and understood. Keep and store away from clothing and other combustible materials. Keep valves and fittings free from grease and oil. Use and store only outdoors or in a well-ventilated place. Wear cold insulating gloves, face shield, and eye protection. In case of fire: Stop leak if safe to do so. Use a backflow preventive device in the piping. Use only the equipment of compatible materials equipment cleaned for oxygen service. DO NOT change or force fit connections. Avoid spills. Do not walk on or roll equipment over spills. Close valve after each use and when empty. Always keep container in upright position. Read and follow the Safety Data Sheet (SDS) before use.

FIRST AID:

IF ON SKIN: Thaw frosted parts with lukewarm water. Do not rub affected area. Get immediate medical advice/attention.

DO NOT REMOVE THIS PRODUCT LABEL

WARNING: For emergency use only when administered by properly trained personnel for oxygen deficiency and resuscitation. For all other medical applications, Rx only.

Uninterrupted use of high concentrations of oxygen over a long duration, without monitoring its effect on oxygen content of arterial blood, may be harmful. Do not attempt to use on patients who have stopped breathing unless used in conjunction of resuscitative equipment. Produced by Air Liquefaction

©Applied Home Healthcare Equipment 2014

Acute Care Gases of CT LLC

23 Nutmeg Valley Road

Wolcott, CT 06716

855-399-1224

Oxygen 15 Cubic Feet

OXYGEN, COMPRESSED USP UN 1072 Produced by Air Liquefaction

OXYGEN 2 133445 (06/19)

WARNING: For emergency use only when administered by properly trained personnel for oxygen deficiency and resuscitation. For all other medical applications, Rx only. Uninterrupted use of high concentrations of oxygen over a long duration, without monitoring its effect on oxygen content of arterial blood, may be harmful. Do not attempt to use on patients who have stopped breathing unless used in conjunction with resuscitative equipment. DANGER: MAY CAUSE OR INTENSIFY FIRE; OXIDIZER. CONTAINS GAS UNDER PRESSURE; MAY EXPLODE IF HEATED. Do not handle until all safety precautions have been read and understood. Keep and store away from clothing and other combustible materials. Keep valves and fittings free from grease and oil. Use and store only outdoors or in a well-ventilated place. In case of fire: Stop leak if safe to do so. Use a backflow preventive device in the piping. Use only with equipment of compatible materials of construction and rated for cylinder pressure. Use only with equipment cleaned for oxygen service. Open valve slowly. Close valve after each use and when empty. Protect from sunlight when ambient temperature exceeds 52°C (125° F). Read and follow the Safety Data Sheet (SDS) before use. CAS 7782-44-7 DO NOT REMOVE THIS PRODUCT LABEL.

CONTENTS: 15 CUBIC FEET

ACG ACUTE CARE GASES OF CT, LLC

ACUTE CARE 23 NUTMEG VALLEY RD • WOLCOTT, CT 06716

GASES 855-399-1224

Oxygen 24 cubic feet

OXYGEN, COMPRESSED USP UN 1072 Produced by Air Liquefaction

217359

OXYGEN 2 133445 (05/25)

WARNING: For emergency use only when administered by properly trained personnel for oxygen deficiency and resuscitation. For all other medical applications, Rx required. Uninterrupted use of high concentrations of oxygen over a long duration, without monitoring its effect on oxygen content of arterial blood, may be harmful. Do not attempt to use on patients who have stopped breathing unless used in conjunction with resuscitative equipment. Keep out of reach of children. Federal law requires that this container be refilled with oxygen USP only by establishments registered as a drug manufacturer in accordance with the Fedeal Food, Drug and Consmetic Act. DANGER: MAY CAUSE OR INTENSIFY FIRE; OXIDIZER. CONTAINS GAS UNDER PRESSURE; MAY EXPLODE IF HEATED. Do not handle until all safety precautions have been read and understood. Keep away from clothing and other combustible materials. Keep valves and fittings free from grease and oil. Use and store only outdoors or in a well-ventilated place. In case of fire: Stop leak if safe to do so. Use a backflow preventive device in the piping. Close valve after each use and when empty. Use only with equipment rated for cylinder pressure.Do not open valve until connected to equippment prepared for use. Open valve slowly. Use only with equipment cleaned for oxygen service. Protect from sunlight when ambient temperature exceeds 52°C (125° F). Read and follow the Safety Data Sheet (SDS) before use. CAS 7782-44-7 DO NOT REMOVE THIS PRODUCT LABEL.

CONTENTS: 24 CUBIC FEET

ACG ACUTE CARE GAS, LLC

23 NUTMEG VALLEY RD • WOLCOTT, CT 06716

855-399-1224

NO SMOKING

NO VAPING

Oxygen Compressed - Wolcott

OXYGEN, COMPRESSED USP UN1072

OXYGEN 2

DANGER:

MAY CAUSE OR INTENSIFY FIRE; OXIDIZER, CONTAINS GAS UNDER PRESSURE; MAY EXPLODE IF HEATED.

Do not handle until all safety precautions have been read and understood. Keep and store away from clothing and other combustible materials. Keep valves and fittings free from grease and oil. Use and store only outdoors or in a well-ventilated place. In case of fire: Stop leak if safe to do so. Use a back flow preventive device in the piping. Use only with equipment of compatible materials of construction and rated for cylinder pressure. Use only with equipment cleaned for oxygen service. Open valve slowly. Close valve after each use and when empty. Protect from sunlight when ambient temperature exceeds 52°C (125°F). Read and follow the Safety Data Sheet (SDS) before use.

DO NOT REMOVE THIS LABEL

WARNING: For emergency use only when administered by properly trained personnel for oxygen deficiency and resuscitation. For all other medical applications. Rx only.

Uninterrupted use of high concentrations of oxygen over a long duration without monitoring its effect on oxygen content of arterial blood, may be harmful. Do not attempt to use on patients who have stopped breathing unless used in conjunction with resuscitative equipment. Produced by Air Liquefaction.

© Applied Home Healthcare Equipment 2014

CAS 7782-44-7

Contents

Size

113 Liters

□ M4

165 Liters

□ M6

255 Liters

□ C

425 Liters

□ D

680 Liters

□ E

7080 Liters

□ H

_____ Liters

□ Other

Acute Care Gases of CT, LLC

23 Nutmeg Valley Road

Wolcott, CT 06716

855-399-1224